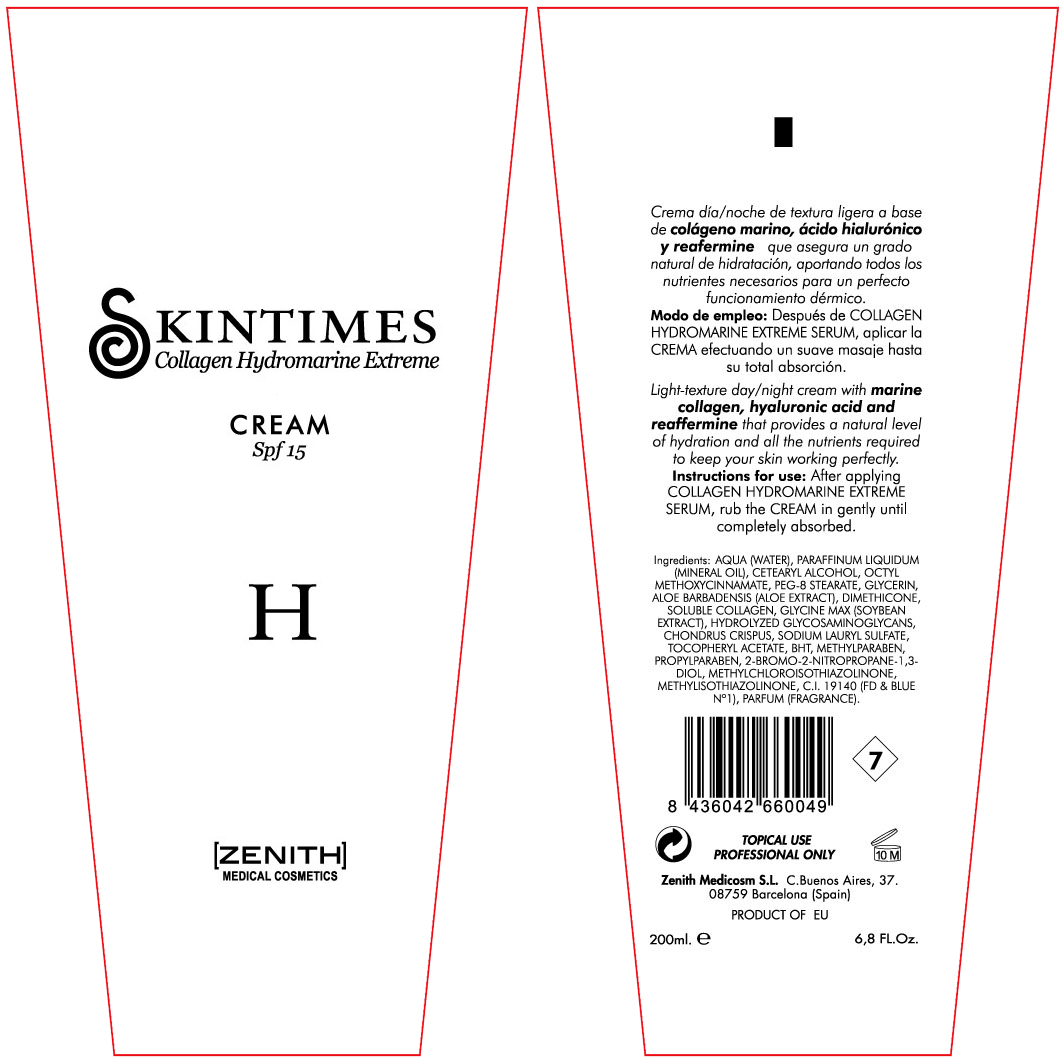 DRUG LABEL: Hydromarine
NDC: 42248-110 | Form: CREAM
Manufacturer: Zenith Medicosm SL
Category: otc | Type: HUMAN OTC DRUG LABEL
Date: 20120121

ACTIVE INGREDIENTS: OCTINOXATE 15 mL/200 mL
INACTIVE INGREDIENTS: ALOE; PROPYLPARABEN; ALPHA-TOCOPHEROL ACETATE; GLYCERIN; TRICHLOROETHANE; SODIUM LAURYL SULFATE; WATER; MINERAL OIL; CETOSTEARYL ALCOHOL; PEG-8 STEARATE; DIMETHICONE; SOYBEAN; CHONDRUS CRISPUS; BUTYLATED HYDROXYTOLUENE; PROPYLPARABEN; BRONOPOL; HYDROLYZED GLYCOSAMINOGLYCANS (BOVINE; 50000 MW); METHYLCHLOROISOTHIAZOLINONE; METHYLPARABEN; COLLAGEN, SOLUBLE, FISH SKIN; FD&C BLUE NO. 1

Drug Facts

Active Ingredient

Octinoxate 7.5%

Description

Light-texture day/night cream with marine collagen, hyaluronic acid and reaffermine that provides a natural level of hydration and all the nutrients required to keep your skin working perfectly.

200ml. 6.8 Fl.Oz.

Warning

TOPICAL USE

PROFESSIONAL ONLY

Instructions for use

After applying COLLAGEN HYDROMARINE EXTREME SERUM, rub the CREAM in gently until absorbed.